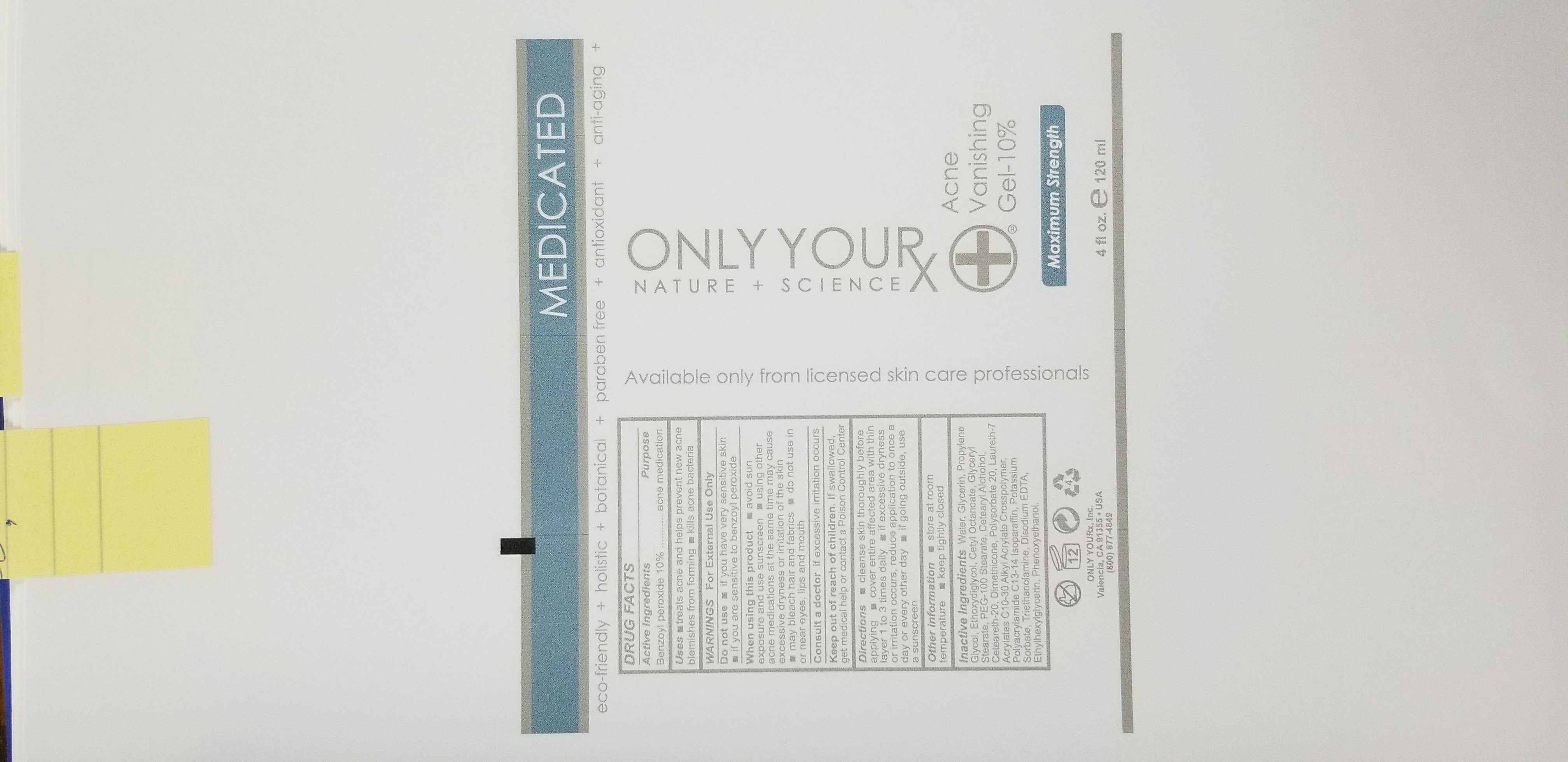 DRUG LABEL: Acne  Vanishing Gel-10%
NDC: 70367-001 | Form: GEL
Manufacturer: Only Yourx Inc.
Category: otc | Type: HUMAN OTC DRUG LABEL
Date: 20200123

ACTIVE INGREDIENTS: BENZOYL PEROXIDE 10 g/100 mL
INACTIVE INGREDIENTS: AMINOMETHYLPROPANOL; MAGNESIUM DISODIUM EDTA; ETHYLHEXYLGLYCERIN; PHENOXYETHANOL; GLYCERIN; PROPYLENE GLYCOL 1-(2-METHYLBUTYRATE); POTASSIUM SORBATE; LAURETH-7; PEG-100 STEARATE; DIMETHICONE; POLYSORBATE 20; C13-14 ISOPARAFFIN

ACTIVE INGREDIENT

10 % Benzoyl peroxide

PURPOSE

To help with the control of acne

DOSAGE AND ADMINISTRATION

- Cleanse skin thoroughly before applying
- Cover entire affected area with thin layer 1 to 3 times daily
- If excessive dryness or irritation occurs, reduce application to once a day or every ther day
- If going outside, use a sunscreen

WARNINGS

WARNING: For external use only

INACTIVE INGREDIENT

Water, Glycerin, Propylene Glycol, Ethoxydiglycol, Cetyl Octanoate, Glyceryl, Stearate, PEG-100 Stearate, Cetearyl Alcohol, Ceteareth-20, Dimthicone, Polysorbate 20, Laureth-7, Acrylates C10-30 Alkyl Acrylate Crosspolymer, Polyacrylamide C3-14 Isoparaffin, Potassium Sorbate, Triethanolamine, Disodium EDTA, Ethylhexylglycerin, Phenooxyethanol

INDICATIONS AND USAGE

Treats acne and helps prevent new acne blemishes from forming

Kills acne bacteria

Keep out of reach of children. If swallowed, get medical help or contact Poison Control Center

OTHER SAFETY INFORMATION

Store at room temperature

Keep tightly closed

Consult a doctor if excessive irritation occurs

Do not use if

- you have very sensitive skin
- if you are sensitive to benzoyl peroxide

When using this product

- avoid sun exposure and use sunscreen
- using other acne medicatons at the same time may cause excessive dryness or irritation of the skin
- may bleach hair and fabrics
- do not use near eyes, lips and mouth